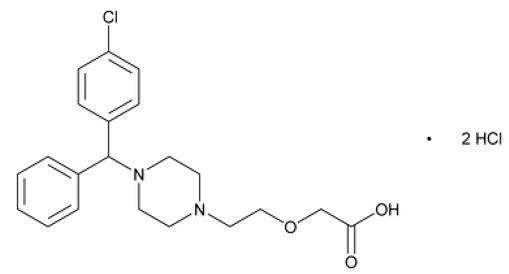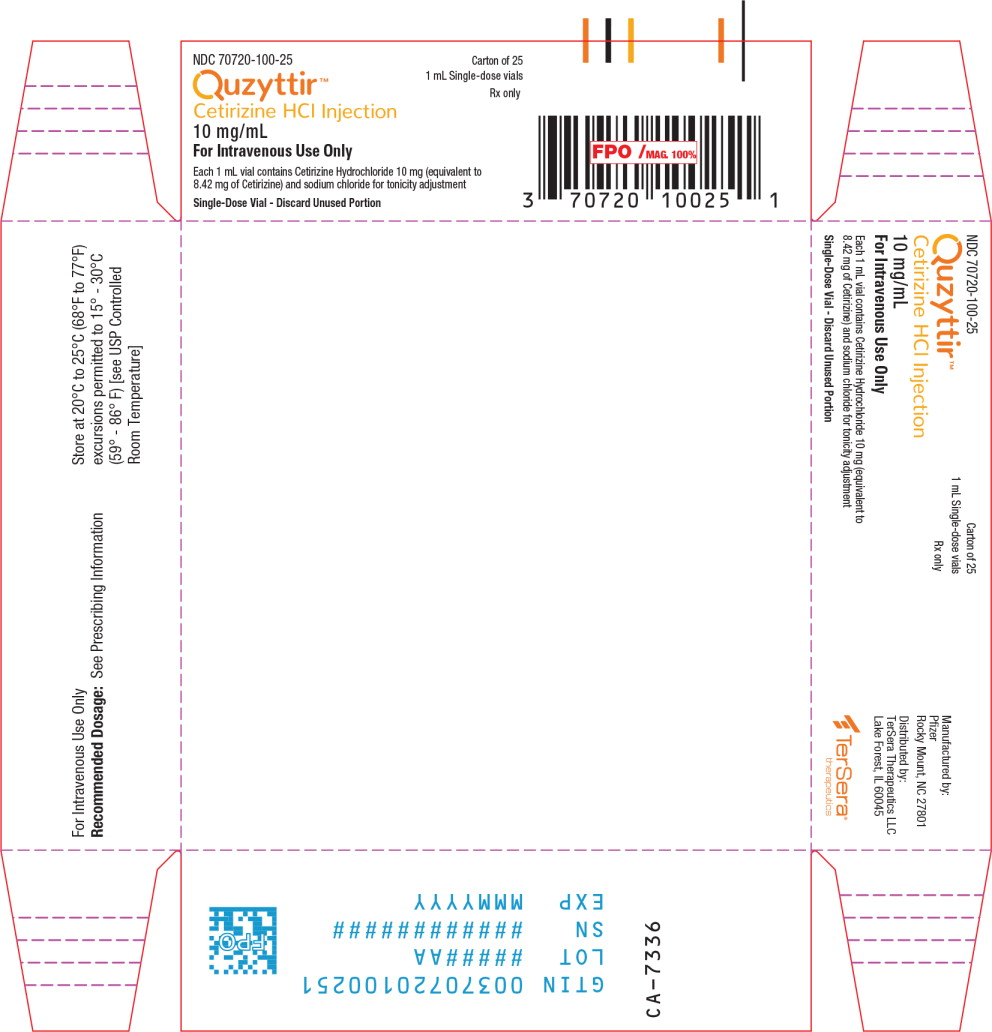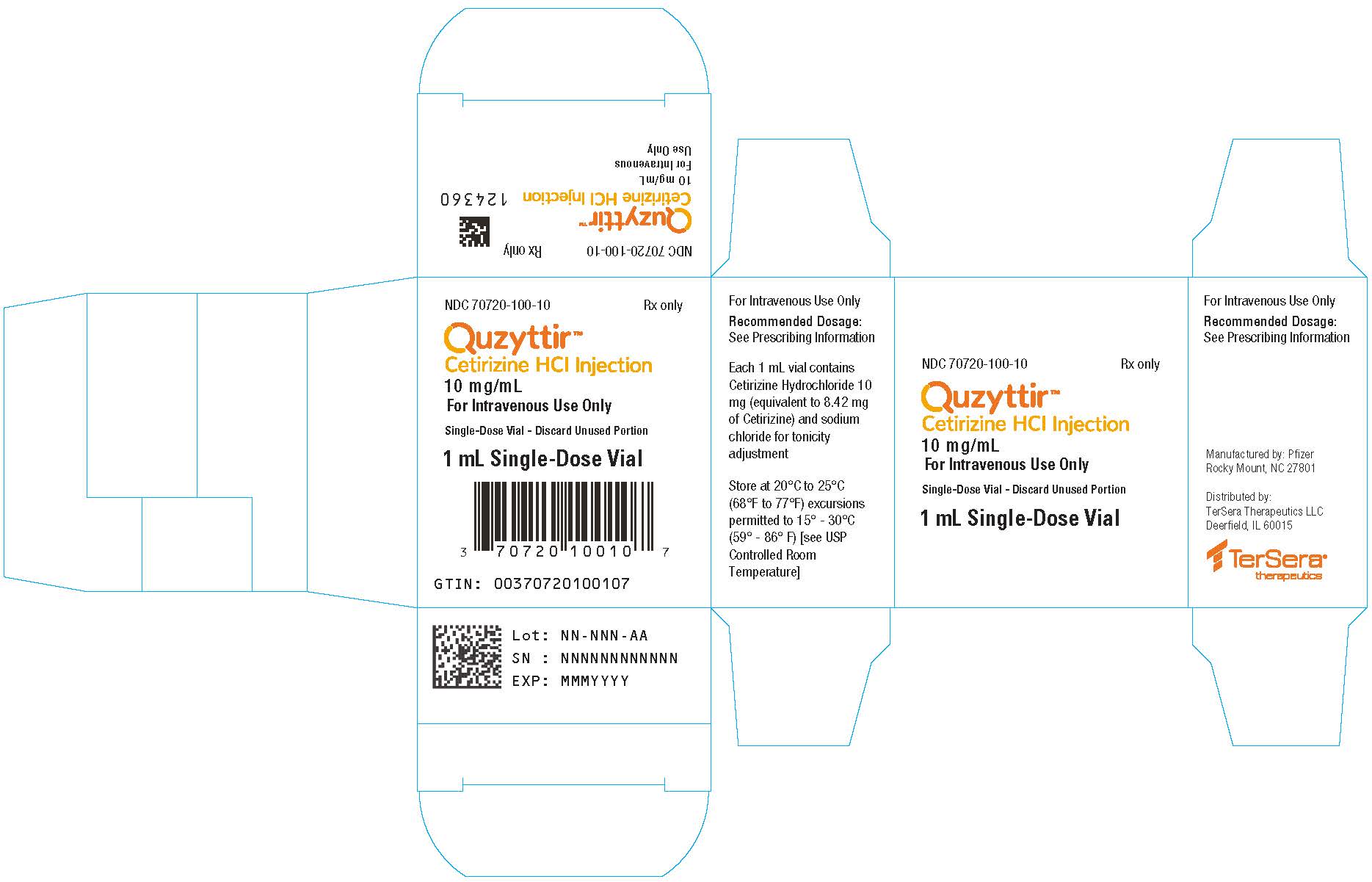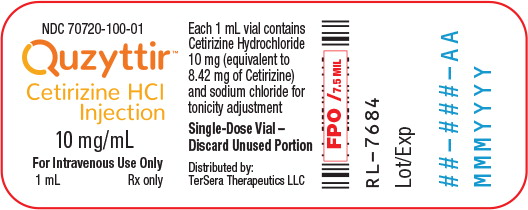 DRUG LABEL: QUZYTTIR
NDC: 70720-100 | Form: INJECTION
Manufacturer: TerSera Therapeutics LLC
Category: prescription | Type: HUMAN PRESCRIPTION DRUG LABEL
Date: 20250728

ACTIVE INGREDIENTS: cetirizine hydrochloride 10 mg/1 mL
INACTIVE INGREDIENTS: Sodium Chloride; Sodium Hydroxide; Hydrochloric Acid; Water

HIGHLIGHTS OF PRESCRIBING INFORMATION

These highlights do not include all the information needed to use QUZYTTIR® safely and effectively. See full prescribing information for QUZYTTIR®.
QUZYTTIR® (cetirizine hydrochloride injection), for intravenous use
Initial U.S. Approval: 1995

1 INDICATIONS AND USAGE

QUZYTTIR® is a histamine-1 (H1) receptor antagonist indicated for the treatment of acute urticaria in adults and children 6 months of age and older (1)

Limitations of Use:

Not recommended in pediatric patients less than 6 years of age with impaired renal or hepatic function (1)

2 DOSAGE AND ADMINISTRATION

For intravenous administration only (2)

Recommended dosages:

- Adults and adolescents ≥ 12 years of age and older: 10 mg (2.1)
- Children 6 to 11 years: 5 mg or 10 mg (2.2)
- Children 6 months to 5 years: 2.5 mg (2.3)

Recommended dosage regimen is once every 24 hours as needed for acute urticaria (2)

3 DOSAGE FORMS AND STRENGTHS

Injection: 10 mg/mL cetirizine hydrochloride (3)

4 CONTRAINDICATIONS

Known hypersensitivity to cetirizine hydrochloride or any of its ingredients, levocetirizine, or hydroxyzine (4)

5 WARNINGS AND PRECAUTIONS

Somnolence/Sedation: Exercise caution when driving a car or operating potentially dangerous machinery (5.1)

6 ADVERSE REACTIONS

The most common adverse reactions (incidence less than 1%) with QUZYTTIR are dysgeusia, headache, paresthesia, presyncope, dyspepsia, feeling hot, and hyperhidrosis.

Most common adverse reactions (incidence equal to or greater than 2%) with use of oral cetirizine hydrochloride are somnolence, fatigue, dry mouth, pharyngitis, and dizziness. (6)

To report SUSPECTED ADVERSE REACTIONS, call TerSera Therapeutics LLC at 1-844-334-4035 or FDA at 1-800-FDA-1088 or www.fda.gov/medwatch.

FULL PRESCRIBING INFORMATION

1 INDICATIONS AND USAGE

QUZYTTIR® is indicated for the treatment of acute urticaria in adults and children 6 months of age and older.

Limitations of use:

QUZYTTIR® is not recommended in pediatric patients less than 6 years of age with impaired renal or hepatic function.

2 DOSAGE AND ADMINISTRATION

QUZYTTIR is a single use injectable product for intravenous administration only. The recommended dosage regimen is once every 24 hours as needed for treatment of acute urticaria. Administer QUZYTTIR as an intravenous push over a period of 1 to 2 minutes. QUZYTTIR is not recommended in pediatric patients less than 6 years of age with impaired renal or hepatic function [see Pediatric Use (8.4)].

If using as an antihistamine prior to infusion product administration, refer to infusion product prescribing information for instructions.

2.1 Adults and adolescents 12 years of age and older

The recommended dosage is 10 mg administered by intravenous injection.

2.2 Children 6 to 11 years of age

The recommended dosage is 5 mg or 10 mg depending on symptom severity administered by intravenous injection.

2.3 Children 6 months to 5 years of age

The recommended dosage is 2.5 mg administered by intravenous injection.

3 DOSAGE FORMS AND STRENGTHS

QUZYTTIR is a sterile, clear, colorless, non-pyrogenic, isotonic aqueous solution of cetirizine hydrochloride for intravenous injection; supplied in 2 mL size amber glass vials for single use. Each 2 mL size amber glass vial contains 1 mL drug solution with 10 mg cetirizine hydrochloride (equivalent to 8.42 mg of cetirizine).

4 CONTRAINDICATIONS

The use of QUZYTTIR is contraindicated in patients with a known hypersensitivity to cetirizine hydrochloride or any of its ingredients, levocetirizine, or hydroxyzine.

5 WARNINGS AND PRECAUTIONS

5.1 Somnolence/Sedation

In clinical trials with QUZYTTIR and cetirizine hydrochloride tablets, the occurrence of somnolence/sedation has been reported in some patients. Exercise due caution when driving a car or operating potentially dangerous machinery. Avoid concurrent use of QUZYTTIR with alcohol or other CNS depressants because additional reduction in alertness and additional impairment of CNS performance may occur.

6 ADVERSE REACTIONS

The following clinically significant adverse reaction is described elsewhere in the labeling:

- Somnolence/Sedation [see Warnings and Precautions (5.1)]

6.1 Clinical Trials Experience

Because clinical trials are conducted under widely varying conditions, adverse reaction rates observed in the clinical trials of a drug cannot be directly compared to rates in the clinical trials of another drug and may not reflect the rates observed in practice.

Oral cetirizine hydrochloride

The following adverse reactions associated with the use of oral cetirizine hydrochloride were identified in clinical trials.

In clinical trials in patients 12 years and older the most common adverse reactions to oral cetirizine hydrochloride occurring with a 2% or greater incidence and greater than placebo were somnolence (14%), fatigue (6%), dry mouth (5%), pharyngitis (2%), and dizziness (2%). In clinical trials in children 6 to 11 years of age with oral cetirizine hydrochloride the most common adverse reactions occurring with a 2% or greater incidence and greater than placebo were headache, pharyngitis, abdominal pain, coughing, somnolence, diarrhea, epistaxis, bronchospasm, nausea, and vomiting. Somnolence appeared to be dose related. Adverse reactions reported in placebo-controlled trials with oral cetirizine hydrochloride in pediatric patients 2 to 5 years were qualitatively similar in nature and generally similar in frequency to those reported in trials with children 6 to 11 years of age. In placebo-controlled trials of pediatric patients 6 to 24 months of age, the incidences of adverse experiences were similar in the oral cetirizine hydrochloride and placebo treatment groups in each trial. In a trial of 1 week duration in children 6 to 11 months of age patients who received oral cetirizine hydrochloride exhibited greater irritability/fussiness than patients on placebo. In a trial of 18 months duration in patients 12 months and older, insomnia occurred more frequently in patients who received oral cetirizine hydrochloride compared to patients who received placebo.

QUZYTTIR

The safety data of QUZYTTIR was evaluated in a randomized, double-blind, single-dose, non-inferiority study comparing QUZYTTIR to intravenous diphenhydramine in 262 adults with acute urticaria.

The adverse reactions with QUZYTTIR occurred at an incidence of less than 1% and include: dyspepsia, feeling hot, dysgeusia, headache, paresthesia, presyncope, and hyperhidrosis.

An additional randomized, double-blind, single dose study was conducted in 33 adults which showed similar safety results.

Sedation

Subject-rated sedation scores were assessed at baseline, 1 hr, and/or 2 hrs, and/or "Readiness for Discharge”. Sedation was rated on a 0 to 3 scale (0 = none, to 3 = severe) with lower sedation scores indicating less sedation. Subjects in the QUZYTTIR treatment group reported less sedation at all time points compared to subjects treated with diphenhydramine.

7 DRUG INTERACTIONS

No clinically significant drug interactions with oral cetirizine hydrochloride, the active ingredient in QUZYTTIR, have been found with theophylline at a low dose, azithromycin, pseudoephedrine, ketoconazole, or erythromycin. There was a small decrease in the clearance of oral cetirizine hydrochloride caused by a 400-mg dose of theophylline; it is possible that larger theophylline doses could have a greater effect [see Clinical Pharmacology (12.3)].

8 USE IN SPECIFIC POPULATIONS

8.1 Pregnancy

Risk Summary

There are no adequate and well-controlled studies in pregnant women with cetirizine hydrochloride the active ingredient in QUZYTTIR. In animal reproduction studies, there was no evidence of fetal harm with administration of cetirizine hydrochloride by the oral route to pregnant mice, rats, and rabbits, during the period of organogenesis, at doses that were 45 times and higher than the maximum recommended human dose (MRHD) in adults. In rats treated during late gestation and the lactation period, cetirizine hydrochloride had no effects on pup development at oral doses up to approximately 30 times the MRHD in adults. In mice treated during late gestation and the lactation period, cetirizine hydrochloride administered by the oral route to the dams had no effects on pup development at a dose that was approximately 10 times the MRHD in adults; however, lower pup weight gain during lactation was observed at a dose that was 45 times the MRHD in adults (See Data). The estimated background risk of major birth defects and miscarriage for the indicated population is unknown. All pregnancies have a background risk of birth defect, loss, or other adverse outcomes. In the U.S. general population, the estimated background risk of major birth defects and miscarriage in clinically recognized pregnancies is 2% to 4% and 15% to 20% respectively.

Data

Animal Data: In embryofetal development studies conducted in mice, rats, and rabbits, cetirizine hydrochloride, administered during the period of organogenesis, was not teratogenic at doses up to 45, 220, and 260 times the MRHD, respectively (on a mg/m^2 basis with maternal oral doses up to 96, 225, and 135 mg/kg).

In a prenatal and postnatal development (PPND) study conducted in mice, cetirizine hydrochloride was administered at oral doses up to 96 mg/kg/day from gestation day 15 through lactation day 21. Cetirizine hydrochloride lowered pup body weight gain during lactation at an oral dose in dams that was approximately 45 times the MRHD (on a mg/m^2 basis with a maternal oral dose of 96 mg/kg/day); however, there were no effects on pup weight gain at an oral dose in dams that was approximately 10 times the MRHD (on a mg/m^2 basis with a maternal oral dose of 24 mg/kg/day). In a PPND study conducted in rats, cetirizine hydrochloride was administered at oral doses up to 180 mg/kg/day from gestation day 17 to lactation day 22. Cetirizine hydrochloride did not have any adverse effects on rat dams or offspring development at doses up to approximately 30 times the MRHD (on a mg/m^2 basis with a maternal oral dose of 30 mg/kg/day). Cetirizine hydrochloride caused excessive maternal toxicity at an oral dose in dams that was approximately 180 times the MRHD (on a mg/m ^2 basis with a maternal oral dose of 180 mg/kg/day).

8.2 Lactation

Risk Summary

Cetirizine hydrochloride has been reported to be present in human breast milk. In mice and beagle dogs, studies indicated that cetirizine hydrochloride was excreted in milk (See Data). When a drug is present in animal milk, it is likely the drug will be present in human milk. The developmental and health benefits of breastfeeding should be considered along with the mother's clinical need for QUZYTTIR and any potential adverse effects on the breastfed child from QUZYTTIR or from the underlying maternal condition.

Data

Animal Data: Cetirizine hydrochloride was detected in the milk of mice. No adverse developmental effects on pups were seen when cetirizine hydrochloride was administered orally to dams during lactation at a dose that was approximately 10 times the MRHD in adults [see Use in Specific Populations (8.1)]. Studies in beagle dogs indicated that approximately 3% of the dose of cetirizine hydrochloride was excreted in milk. The concentration of drug in animal milk does not necessarily predict the concentration of drug in human milk.

8.4 Pediatric Use

The safety and efficacy of QUZYTTIR have been established in patients 6 months to 17 years of age. The efficacy of QUZYTTIR for the treatment of acute urticaria down to 6 months of age is based on extrapolation of the efficacy of QUZYTTIR in adults with acute urticaria [see Clinical Studies (14)] and supported by pharmacokinetic data with oral cetirizine hydrochloride (the active ingredient in QUZYTTIR) in patients 6 months to 17 years of age. Based upon the known PK profile of oral cetirizine hydrochloride, the exposure of IV cetirizine hydrochloride in pediatric patients (6 months to 17 years of age) is expected to be similar to the exposure of IV cetirizine hydrochloride in adults at the labeled doses. Extrapolation of efficacy is based on the likelihood that the disease course, pathophysiology and the drug's effect are similar between these two populations.

The safety of QUZYTTIR in children 6 months to 17 years of age is supported by safety information from placebo-controlled clinical trials with oral cetirizine hydrochloride in patients 6 months of age and older [see Adverse Reactions (6)]. QUZYTTIR demonstrates a higher Cmax compared to oral cetirizine hydrochloride in adults [see Clinical Pharmacology (12.3)]. As QUZYTTIR is indicated for an acute condition administered in a medically supervised setting, the safety for higher Cmax in children 6 months to less than 18 years of age is supported by the safety data from the clinical trial with IV cetirizine hydrochloride in adults [see Adverse Reactions (6)] and available safety information from pediatric overdose cases.

Because of the absence of pharmacokinetic and safety information for cetirizine hydrochloride in children below 6 years of age with impaired renal or hepatic function, the use of QUZYTTIR in this impaired patient population is not recommended [see Dosage And Administration (2)].

The safety and efficacy of QUZYTTIR in patients less than 6 months of age has not been established.

8.5 Geriatric Use

In clinical trials with QUZYTTIR, 18 patients were 65 years and older, and 6 patients were 75 years and older. No overall differences in safety were observed between these patients and younger patients, but greater sensitivity of some older individuals cannot be ruled out. In clinical trials with cetirizine hydrochloride oral tablets, 186 patients were 65 years and older, and 39 patients were 75 years and older. No overall differences in safety were observed between these patients and younger patients.

With regard to efficacy, the clinical trials with cetirizine hydrochloride oral tablets and QUZYTTIR did not include sufficient numbers of patients aged 65 years and older to determine whether they respond differently than younger patients.

8.6 Hepatic Impairment

No dosage adjustment is required in patients with hepatic impairment. Monitor for antihistaminic side effects in this patient population [see Clinical Pharmacology (12.3)].

8.7 Renal Impairment

No dosage adjustment is required in patients with moderate and severe renal impairment and in patients on dialysis. Monitor for antihistaminic side effects in this patient population [see Clinical Pharmacology (12.3)].

10 OVERDOSAGE

Cases of adult and pediatric patients with overdoses of only oral cetirizine hydrochloride have been reported, some of which resulted in adverse reactions. Adult overdose cases involved patients 18 to 81 years of age receiving oral cetirizine hydrochloride doses of 70 mg to 800 mg (7 to 80 times the maximum recommended dosage of 10 mg/day in adults). The most commonly reported adverse reactions were somnolence and fatigue. Other reported adverse reactions included tachycardia, abdominal pain, nausea, and vomiting. Pediatric overdose cases involved patients 18 months to 15 years of age receiving oral cetirizine hydrochloride doses of 90 mg to 300 mg (9 to 72 times the maximum age recommended dose). The adverse reactions reported included: somnolence, difficulty walking, agitation/irritability, hard to swallow/articulate clearly, tachycardia, vomiting, mydriasis, and elevated creatinine phosphokinase.

If overdose with QUZYTTIR occurs, treatment should be symptomatic or supportive, taking into account any concomitantly ingested medications. There is no known specific antidote to cetirizine hydrochloride. Cetirizine hydrochloride is not effectively removed by dialysis, and dialysis will be ineffective unless a dialyzable agent has been concomitantly ingested.

11 DESCRIPTION

Cetirizine hydrochloride, the active component of QUZYTTIR, is a selective histamine-1 (H1) receptor antagonist. The chemical name is (±) –[2-[4-[(4-chlorophenyl)phenylmethyl]-1- piperzinyl] ethoxy]acetic acid, dihydrochloride. Cetirizine hydrochloride is a racemic compound with an empirical formula of C21H25ClN2O3•2HCl. The molecular weight is 461.82 and the chemical structure is shown below:

Cetirizine hydrochloride is a white, crystalline powder and is water soluble. QUZYTTIR is a sterile, clear, colorless, non-pyrogenic, isotonic solution for intravenous injection. Each mL of QUZYTTIR injection contains 10 mg cetirizine hydrochloride (equivalent to cetirizine 8.42 mg) and 6.5 mg sodium chloride, USP to adjust solution tonicity, in water for injection, USP. QUZYTTIR is supplied in 2 mL size amber glass vials for single use. Each 2 mL size amber glass vial contains 1 mL drug solution with 10 mg cetirizine hydrochloride (10 mg/mL). QUZYTTIR's pH is maintained between 4.5 to 6.5 with sodium hydroxide and/or hydrochloric acid as needed. The osmolality of QUZYTTIR injection is between 255 to 340 mOsmol.

12 CLINICAL PHARMACOLOGY

12.1 Mechanism of Action

Cetirizine hydrochloride, a human metabolite of hydroxyzine, is an antihistamine; its principal effects are mediated via selective inhibition of peripheral H1-receptors. The antihistaminic activity of cetirizine hydrochloride has been clearly documented in a variety of animal and human models. In vivo and ex vivo animal models have shown negligible anticholinergic and antiserotonergic activity. In clinical studies however, dry mouth was more common with cetirizine hydrochloride than with placebo. In vitro receptor binding studies have shown no measurable affinity for receptors other than H1 receptors.

12.2 Pharmacodynamics

Studies in 69 adult normal volunteers (aged 20 to 61 years) showed that cetirizine hydrochloride oral tablets at doses of 5 and 10 mg strongly inhibited the skin wheal and flare caused by the intradermal injection of histamine. The onset of this activity after a single 10-mg oral dose occurred within 20 minutes in 50% of subjects and within one hour in 95% of subjects; this activity persisted for at least 24 hours. Cetirizine hydrochloride tablets at doses of 5 and 10 mg also strongly inhibited the wheal and flare caused by intradermal injection of histamine in 19 pediatric volunteers (aged 5 to 12 years) and the activity persisted for at least 24 hours. In a 35-day study in children aged 5 to 12, no tolerance to the antihistaminic (suppression of wheal and flare response) effects of cetirizine hydrochloride oral tablets was found. In 10 infants 7 to 25 months of age who received 4 to 9 days of cetirizine hydrochloride in an oral solution (0.25 mg/kg bid), there was a 90% inhibition of histamine-induced (10 mg/mL) cutaneous wheal and 87% inhibition of the flare 12 hours after administration of the last dose. The clinical relevance of this suppression of histamine-induced wheal and flare response on skin testing is unknown.

The effects of intradermal injection of various other mediators or histamine releasers were also inhibited by oral cetirizine hydrochloride, as was response to a cold challenge in patients with cold-induced urticaria. In mildly asthmatic subjects, cetirizine hydrochloride oral tablets at 5 to 20 mg blocked bronchoconstriction due to nebulized histamine, with virtually total blockade after a 20-mg dose. In studies conducted for up to 12 hours following cutaneous antigen challenge, the late phase recruitment of eosinophils, neutrophils and basophils, components of the allergic inflammatory response, was inhibited by cetirizine hydrochloride oral tablets at a dose of 20 mg.

Cardiac Electrophysiology

In four clinical studies in healthy adult males, no clinically significant mean increases in QTc were observed in subjects treated with cetirizine hydrochloride oral tablets. In the first study, a placebo-controlled crossover trial, cetirizine hydrochloride oral tablets were given at doses up to 60 mg per day, 6 times the maximum clinical dose, for 1 week, and no significant mean QTc prolongation occurred. In the second study, a crossover trial, cetirizine hydrochloride oral tablets 20 mg and erythromycin (500 mg every 8 hours) were given alone and in combination. There was no significant effect on QTc with the combination or with cetirizine hydrochloride alone. In the third trial, also a crossover study, cetirizine hydrochloride oral tablet 20 mg and ketoconazole (400 mg per day) were given alone and in combination. Cetirizine caused a mean increase in QTc of 9.1 msec from baseline after 10 days of therapy. Ketoconazole also increased QTc by 8.3 msec. The combination caused an increase of 17.4 msec, equal to the sum of the individual effects. Thus, there was no significant drug interaction on QTc with the combination of cetirizine and ketoconazole. In the fourth study, a placebo-controlled parallel trial, cetirizine hydrochloride oral tablet 20 mg was given alone or in combination with azithromycin (500 mg as a single dose on the first day followed by 250 mg once daily). There was no significant increase in QTc with cetirizine hydrochloride 20 mg alone or in combination with azithromycin.

In a four-week clinical trial in pediatric patients aged 6 to 11 years, results of randomly obtained ECG measurements before treatment and after 2 weeks of treatment showed that cetirizine hydrochloride oral tablet 5 or 10 mg did not increase QTc versus placebo. In a one week clinical trial (N=86) of cetirizine hydrochloride oral syrup (0.25 mg/kg bid) compared with placebo in pediatric patients 6 to 11 months of age, ECG measurements taken within 3 hours of the last dose did not show any ECG abnormalities or increases in QTc interval in either group compared to baseline assessments. Data from other studies where cetirizine hydrochloride oral was administered to patients 6-23 months of age were consistent with the findings in this study.

The effects of cetirizine hydrochloride on the QTc interval at doses higher than 10 mg have not been studied in children less than 12 years of age.

12.3 Pharmacokinetics

In a single dose crossover study in healthy volunteers under fasting conditions, cetirizine reached a mean Cmax of 495 ng/mL and 1344 ng/mL following single dose intravenous (IV) administration of 5 mg and 10 mg, respectively, injected over a period of 1 to 1.5 minutes. Peak concentrations were reached at 0.06 hour (range 0.03 to 0.07 hour) and 0.03 hour (range 0.03 to 2.00 hour) for cetirizine hydrochloride 5 mg and 10 mg IV injection, respectively. The mean systemic exposure (AUC0-inf) for cetirizine hydrochloride 5 mg and 10 mg IV injection was 1318 ng·hr/mL and 2746 ng·hr/mL, respectively. The AUC0-inf for cetirizine hydrochloride 10 mg oral tablet in the study was 2651 ng·hr/mL.

Absorption

Following oral administration of tablets or syrup in adults, cetirizine was rapidly absorbed with a time to maximum concentration (Tmax) of approximately 1 hour. When healthy volunteers were administered multiple doses of cetirizine hydrochloride (10 mg oral tablets once daily for 10 days), a mean peak plasma concentration (Cmax) of 311 ng/mL was observed and there was no accumulation. Cetirizine pharmacokinetics were linear for oral doses ranging from 5 to 60 mg. Food had no effect on the extent of cetirizine exposure (AUC) but Tmax was delayed by 1.7 hours and Cmax was decreased by 23% in the presence of food when cetirizine hydrochloride was administered orally.

Distribution

The mean plasma protein binding of cetirizine is 93%, independent of concentration in the range of 25-1000 ng/mL, which includes the therapeutic plasma levels observed.

Elimination

The mean elimination half-life in 146 healthy volunteers across multiple pharmacokinetic studies was 8.3 hours and the apparent total body clearance for cetirizine was approximately 53 mL/min.

Metabolism

Cetirizine is metabolized to a limited extent by oxidative O-dealkylation to a metabolite with negligible antihistaminic activity. The enzyme or enzymes responsible for this metabolism have not been identified.

Excretion

A mass balance study in 6 healthy male volunteers indicated that 70% of the administered radioactivity was recovered in the urine and 10% in the feces. Approximately 50% of the radioactivity was identified in the urine as unchanged drug. Most of the rapid increase in peak plasma radioactivity was associated with parent drug, suggesting a low degree of first-pass metabolism.

Specific Populations

Geriatric Patients: Following a single, 10-mg oral dose, the elimination half-life was prolonged by 50% and the apparent total body clearance was 40% lower in 16 geriatric subjects with a mean age of 77 years compared to 14 adult subjects with a mean age of 53 years. The decrease in cetirizine clearance in these elderly volunteers may be related to decreased renal function.

Pediatric Patients: When pediatric patients aged 7 to 12 years received a single, 5-mg oral cetirizine hydrochloride capsule, the mean Cmax was 275 ng/mL. Based on cross-study comparisons, the weight-normalized, apparent total body clearance was 33% greater and the elimination half-life was 33% shorter in this pediatric population than in adults. In pediatric patients aged 2 to 5 years who received 5 mg oral tablets of cetirizine hydrochloride, the mean Cmax was 660 ng/mL. Based on cross-study comparisons, the weight-normalized apparent total body clearance was 81 to 111% greater and the elimination half-life was 33 to 41% shorter in this pediatric population than in adults. In pediatric patients aged 6 to 23 months who received a single dose of 0.25 mg/kg cetirizine hydrochloride oral solution (mean dose 2.3 mg), the mean Cmax was 390 ng/mL. Based on cross-study comparisons, the weight-normalized, apparent total body clearance was 304% greater and the elimination half-life was 63% shorter in this pediatric population compared to adults. The average AUC (0-t) in children 6 months to less than 2 years of age receiving the maximum dose of cetirizine hydrochloride oral solution (2.5 mg twice a day) is expected to be two-fold higher than that observed in adults receiving a dose of 10 mg cetirizine hydrochloride oral tablets once a day.

Male and Female Patients: The effect of gender of cetirizine pharmacokinetics has not been adequately studied.

Racial or Ethnic Groups: No race-related difference in the kinetics of cetirizine has been observed.

Patients with Renal Impairment: The kinetics of cetirizine were studied following multiple, oral, 10-mg daily doses of cetirizine hydrochloride for 7 days in 7 normal volunteers (creatine clearance 89-128 mL/min), 8 patients with mild renal function impairment (creatinine clearance 42-77 mL/min) and 7 patients with moderate renal function impairment (creatine clearance 11-31 mL/min). The pharmacokinetics of oral cetirizine were similar in patients with mild impairment and normal volunteers. Moderately impaired patients had a 3-fold increase in half-life and a 70% decrease in clearance compared to normal volunteers. Patients on hemodialysis (n =5) given a single, 10-mg oral dose of cetirizine hydrochloride had a 3-fold increase in half-life and a 70% decrease in clearance compared to normal volunteers. Less than 10% of the administered dose was removed during the single dialysis session.

The pharmacokinetics of IV cetirizine has not been evaluated in patients with renal impairment.

Patients with Hepatic Impairment: Sixteen patients with chronic liver diseases (hepatocellular, cholestatics, and biliary cirrhosis), given 10 or 20 mg of cetirizine hydrochloride as a single oral dose had a 50% increase in half-life along with a corresponding 40% decrease in clearance compared to 16 healthy subjects.

The pharmacokinetics of IV cetirizine has not been evaluated in patients with hepatic impairment.

Drug Interaction Studies

No interactions were observed in pharmacokinetic interaction studies conducted with oral cetirizine hydrochloride and pseudoephedrine, antipyrine, ketoconazole, erythromycin and azithromycin. In a multiple dose study of theophylline (400 mg once daily for 3 days) and cetirizine hydrochloride (20 mg oral tablets once daily for 3 days), a 16% decrease in the clearance of cetirizine was observed. The disposition of theophylline was not altered by concomitant cetirizine hydrochloride administration.

13 NONCLINICAL TOXICOLOGY

13.1 Carcinogenesis, Mutagenesis, Impairment of Fertility

Carcinogenesis

In a 2-year carcinogenicity study in rats, cetirizine hydrochloride was not carcinogenic at dietary doses up to 20 mg/kg (approximately 20, 10, 25, and 6 times the MRHDs in adults, children 6 to 11 years of age, children 2 to 5 years of age, and children 6 months to less than 2 years of age, respectively, on a mg/m^2 basis). In a 2-year carcinogenicity study in mice, cetirizine hydrochloride caused an increased incidence of benign hepatic tumors in males at a dietary dose of 16 mg/kg (approximately 8, 4, 9, and 2 times the MRHDs in adults, children 6 to 11 years of age, children 2 to 5 years of age, and children 6 months to less than 2 years of age, respectively, on a mg/m^2 basis). No increased incidence of benign hepatic tumors was observed in mice at a dietary dose of 4 mg/kg (approximately 2, 1, 2, and 0.5 times the MRHDs in adults, children 6 to 11 years of age, children 2 to 5 years of age, and children 6 months to less than 2 years of age, respectively, on a mg/m ^2 basis). The clinical significance of these findings during long-term use of QUZYTTIR is not known.

Mutagenesis

Cetirizine hydrochloride was not mutagenic in the Ames test, and not clastogenic in the human lymphocyte assay, the mouse lymphoma assay, and in vivo micronucleus test in rats.

Impairment of Fertility

Fertility and reproductive performance were unaffected in male and female mice and rats that received cetirizine hydrochloride at oral doses up to 64 and 200 mg/kg/day, respectively (approximately 30 and 190 times the MRHD in adults on a mg/m^2 basis).

14 CLINICAL STUDIES

The safety and efficacy of QUZYTTIR for the treatment of acute urticaria was demonstrated in a randomized, active-controlled, double-blind, single dose, multicenter (US and Canada), parallel group trial in 262 patients 18 years of age and older presenting to Emergency Departments or Urgent care Centers (NCT02935699). Subjects were treated with 10 mg of QUZYTTIR or 50 mg diphenhydramine injection. Patients with acute urticaria with or without other diseases were enrolled, including patients with concomitant angioedema. The majority of the patients were Caucasian (48%) and female (63%) with a mean age of 39 years.

The primary efficacy endpoint was the change from baseline in patient-rated pruritus score assessed 2 hrs post treatment for the intent-to-treat (ITT) population. Pruritus was graded on a severity score of 0 to 3 with 0 = no pruritus, 1 = mild, 2 =moderate, and 3 = severe. The trial was non-inferiority design with the pre-specified non-inferiority margin of 0.50 for the difference between treatment groups. Two key secondary efficacy outcome measures: (i) the need to return to any ED or clinic after patient discharge, and (ii) time spent at the treatment center (time from treatment administration to readiness for discharge) were adjusted for multiplicity.

Result for the change from baseline in the pruritus scores are shown in Table 1. The difference between treatment groups excluded the pre-specified non-inferiority margin, i.e. the lower bound of the 95% confidence interval for the difference of diphenhydramine minus QUZYTTIR did not include – 0.50. The primary efficacy data are presented in Table 1.

Table 1. Primary Efficacy Endpoint: Patient-rated Pruritus Score Change from Baseline at 2 hrs (using LOCF); ITT population
 | Diphenhydramine injection 50 mg (N = 135) | QUZYTTIR injection 10 mg (N = 127) | Adjusted Difference between treatment (95% CI)
Baseline: mean (SD) | 2.19 (0.748) | 2.20 (0.727)
Change from Baseline: mean (SD) | -1.50 (0.984) | -1.61 (0.944) | 0.06 (-0.28, 0.40)*
LOCF: last observation carried forward; ITT: intent-to-treat
*Since the lower bound of the 95% CI for the treatment difference was > -0.50, effectiveness of QUZYTTIR injection was demonstrated to be non-inferior to the effectiveness of diphenhydramine injection. The treatment difference and 95% CI were obtained from a generalized linear mixed-effects model. The model consisted of the change from baseline at 2 hours as the dependent variable and site, treatment and site-by-treatment interaction as the fixed effect.

Additionally, in this trial the proportion of patients returning to any emergency department or clinic was lower in the QUZYTTIR treatment group (6%) compared to the diphenhydramine treatment group (14%), and the time spent in the treatment center (hours spent reported as mean (SD) was shorter in the QUZYTTIR treatment group (1.7 (0.9)) compared to the diphenhydramine treatment group (2.1 (1.1)).

16 HOW SUPPLIED/STORAGE AND HANDLING

QUZYTTIR (cetirizine hydrochloride injection), 10 mg/mL, pH between 4.5 to 6.5, is supplied as a sterile, clear, colorless, non-pyrogenic isotonic aqueous solution in single-use 2 mL amber glass vials. The following packaging configuration is available:

- NDC 70720-100-01: 10 mg/mL cetirizine hydrochloride single-use vial
- NDC 70720-100-10: Carton containing 1 single-use vial (10 mg/mL cetirizine hydrochloride)
- NDC 70720-100-25: Carton containing 25 single-use vials (10 mg/mL cetirizine hydrochloride)

Storage and Handling:

QUZYTTIR (cetirizine hydrochloride injection) should be stored at 20°C to 25°C (68°F to 77°F), excursions permitted to 15° - 30°C (59° - 86°F) [see USP Controlled Room Temperature].

Discard unused portion.

17 PATIENT COUNSELING INFORMATION

Somnolence/Sedation

Inform patients that somnolence has occurred with administration of QUZYTTIR. Instruct patients to exercise caution when driving a car or operating potentially dangerous machinery. Instruct patients to avoid use of alcohol or other CNS depressants after they have received treatment with QUZYTTIR because additional reduction in alertness and additional impairment of CNS performance might occur [see Warnings and Precautions (5.1)].

QUZYTTIR® is a registered trademark of TerSera Therapeutics LLC or its affiliates.

Distributed by: TerSera Therapeutics LLC, Deerfield, IL 60015
©2025 TerSera Therapeutics LLC

U.S. Patent Numbers:
9,119,771; 8,263,581; 8,513,259; 8,314,083; 9,180,090

Principal Display Panel – Carton Label

NDC 70720-100-25

Quzyttir™

Cetirizine HCl Injection

10 mg/mL

For Intravenous Use Only

Each 1 mL vial contains Cetirizine Hydrochloride 10 mg (equivalent to
8.42 mg of Cetirizine) and sodium chloride for tonicity adjustment

Single-Dose Vial - Discard Unused Portion

Carton of 25

1 mL Single-dose vials

Rx only

Principal Display Panel – Carton Label

NDC 70720-100-10 Rx only

Quzyttir™

Cetirizine HCl Injection

10 mg/mL

For Intravenous Use Only

Single-Dose Vial - Discard Unused Portion

1 mL Single-Dose Vial

Principal Display Panel – Vial Label

NDC 70720-100-01

Quzyttir™

Cetirizine HCl
Injection

10 mg/mL

For Intravenous Use Only

1 mL

Rx Only

Each 1 mL vial contains
Cetirizine Hydrochloride
10 mg (equivalent to
8.42 mg of Cetirizine)
and sodium chloride for
tonicity adjustment

Single-Dose Vial -
Discard Unused Portion

Distributed by:
TerSera Therapeutics LLC